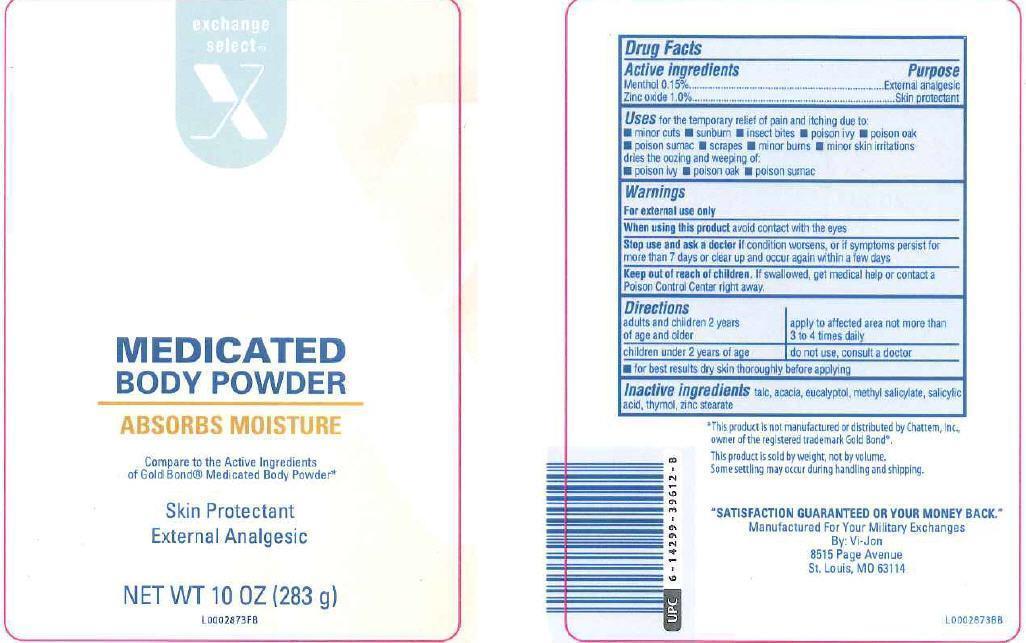 DRUG LABEL: Medicated
NDC: 55301-551 | Form: POWDER
Manufacturer: Your Military Exchange
Category: otc | Type: HUMAN OTC DRUG LABEL
Date: 20130118

ACTIVE INGREDIENTS: MENTHOL 1.5 mg/1 g; ZINC OXIDE 10 mg/1 g
INACTIVE INGREDIENTS: TALC; ACACIA; EUCALYPTOL; METHYL SALICYLATE; SALICYLIC ACID; THYMOL; ZINC STEARATE

Drug Facts

Active ingredients

Menthol 0.15%

Zinc Oxide 1.0%

Purpose

Exteranal analgesic

Skin protectant

Use

Uses for temporary relief of pain and itching due to:

- minor cuts
- sunburn
- insects bites
- poison ivy
- poison oak
- poison sumac
- scrapes
- minor burns
- minor skin iritations

dries the oozing and weeping of

- poison ivy
- poison oak
- poison sumac

Warnings

For external use only

When using this product avoid contact with the eyes

Stop use and ask a doctor if condition worsens, or if symptoms persist for more than 7 days or clear up and occur again within a few days

Keep out of reach of children. If swallowed, get medical help or contact a Poison Control Center right away.

Directions

adults and children 2 years of age and older - apply to affected area not more than 3 to 4 times daily

children under 2 years of age - do not use, consult a doctor

- for best results dry skin thoroughly before applying

Inactive ingredients

Inactive ingredients talc, acacia, eucaluptol, methyl salicylate, salicylic acid, thymol, zinc stearate

Disclaimer

This product is not manufactured or distributed by Chattem, Inc., owner of the regstered trademark Gold Bond.

This product is sold by weight, not by volume. Some settling may occure during handling and shipping.

Adverse Reaction

SATISFACTION GUARANTEED OR YOUR MONEY BACK

Manufactured For Your Military Exchanges

By: Vi-Jon

8515 Page Avenue

St. Louis, MO 63114

Principal display panel

Exchange

Select

MEDICATED

BODY POWDER

ABSORBS MOISTURE

Compare to the Active Ingredients

of Gold Bond medicated Body Powder

Skin Protectant

External Analgesic

NET WT 10 OZ (283 g)